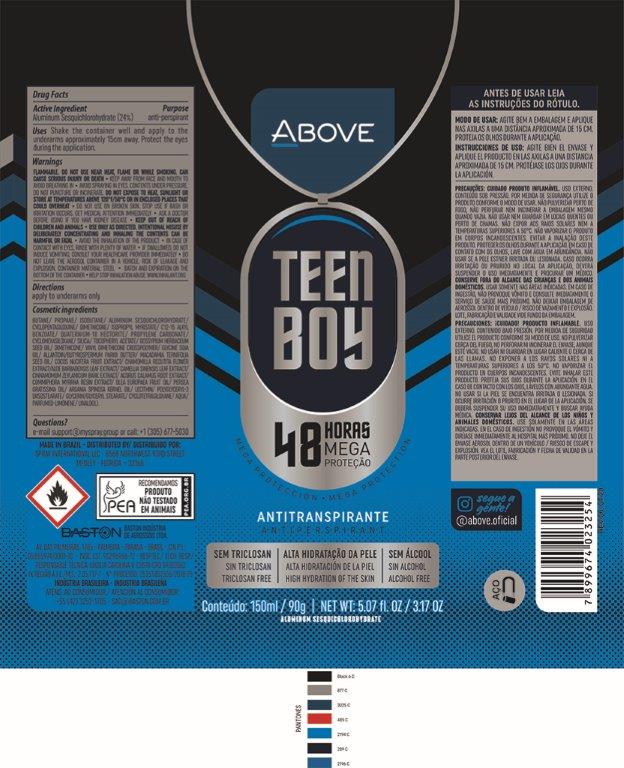 DRUG LABEL: Antiperspirant Above Teen Boy
NDC: 73306-1109 | Form: AEROSOL, SPRAY
Manufacturer: Baston Industria de Aerossóis Ltda
Category: otc | Type: HUMAN OTC DRUG LABEL
Date: 20241226

ACTIVE INGREDIENTS: ALUMINUM SESQUICHLOROHYDRATE 24 g/100 g
INACTIVE INGREDIENTS: SILICA DIMETHYL SILYLATE; COCONUT; ALLANTOIN; ACORUS CALAMUS ROOT; DISTEARDIMONIUM HECTORITE; CYCLOMETHICONE 5; PROPYLENE CARBONATE; ARGAN OIL; ISOPROPYL MYRISTATE; AVOCADO OIL; GREEN TEA LEAF; MACADAMIA OIL; SHEA BUTTER; GLYCERYL MONOSTEARATE; ALOE VERA LEAF; MYRRH OIL; DIMETHICONE; GLYCERIN; ISOBUTANE; BUTANE; LECITHIN, SOYBEAN; CINNAMON BARK OIL; .ALPHA.-TOCOPHEROL ACETATE; VINYL DIMETHICONE/METHICONE SILSESQUIOXANE CROSSPOLYMER; WATER; POLYGLYCERYL-3 DIISOSTEARATE; PROPANE; LEVANT COTTON SEED

Antiperspirant Above Teen Boy Aerosol